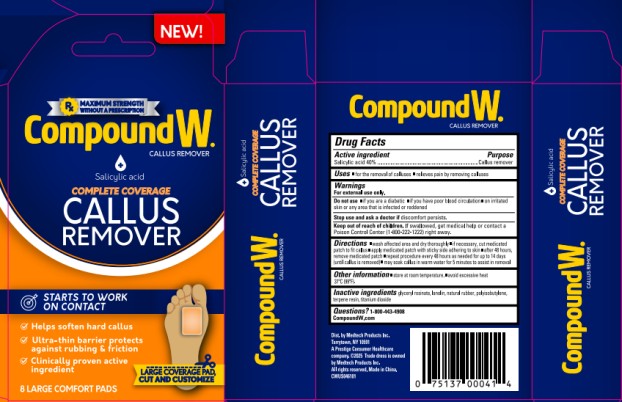 DRUG LABEL: Compound W Complete Coverage Callus Remover
NDC: 63029-624 | Form: PLASTER
Manufacturer: Medtech Products Inc.
Category: otc | Type: HUMAN OTC DRUG LABEL
Date: 20251030

ACTIVE INGREDIENTS: SALICYLIC ACID 0.4 g/1 1
INACTIVE INGREDIENTS: GLYCERYL ROSINATE; LANOLIN; NATURAL LATEX RUBBER; POLYISOBUTYLENE (1300 MW); TERPENE RESIN; TITANIUM DIOXIDE

Compound W Complete Coverage Callus Remover 63029-624-08

Drug Facts

Active ingredient

Salicylic acid 40%

Purpose

Callus remover

Uses

- for the removal of calluses
- relieves pain by removing calluses

Warnings

For external use only.

Do not use

- if you are a diabetic
- if you have poor blood circulation
- on irritated skin or any area that is infected or reddened

Stop use and ask a doctor if

discomfort persists.

Keep out of reach of children.

If swallowed, get medical help or contact a Poison Control Center (1-800-222-1222) right away.

Directions

- wash affected area and dry thoroughly
- if necessary, cut medicated patch to fit callus
- apply medicated patch with sticky side adhering to skin
- after 48 hours, remove medicated patch
- repeat procedure every 48 hours as needed for up to 14 days (until callus is removed)
- may soak callus in warm water for 5 minutes to assist in removal

Other information

- store at room temperature. avoid excessive heat 37ºC(99ºF).

Inactive ingredients

glyceryl rosinate, lanolin, natural rubber, polyisobutylene, terpene resin, titanium dioxide

Questions?

1-800-443-4908

CompoundW.com

Dist. by Medtech Products Inc.

Tarrytown, NY 10591

A Prestige Consumer Healthcare

company. ©2025 Trade dress is owned

by Medtech Products Inc. All rights

reserved. Made in China.

CWUS046101